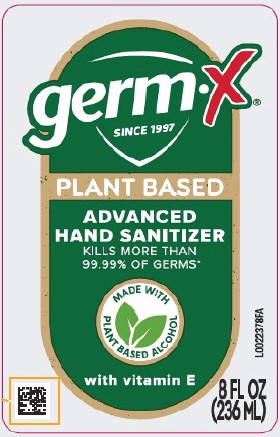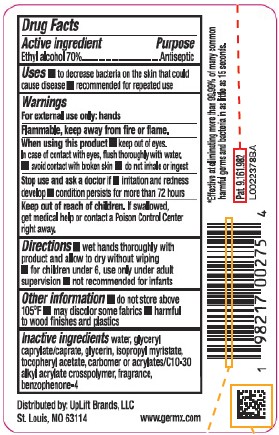 DRUG LABEL: Hand Sanitizer
NDC: 83986-529 | Form: GEL
Manufacturer: UpLift Brands LLC
Category: otc | Type: HUMAN OTC DRUG LABEL
Date: 20251103

ACTIVE INGREDIENTS: ALCOHOL 70 mL/100 mL
INACTIVE INGREDIENTS: WATER; GLYCERYL CAPRYLATE/CAPRATE; GLYCERIN; ISOPROPYL MYRISTATE; .ALPHA.-TOCOPHEROL ACETATE; CARBOMER HOMOPOLYMER, UNSPECIFIED TYPE; CARBOMER COPOLYMER TYPE B (ALLYL PENTAERYTHRITOL CROSSLINKED); SULISOBENZONE

Germ-X 529.000/529AA rev 1
Advanced Hand Sanitizer Original Scent

Active Ingredient

Ethyl alcohol 70%

Purpose

Antiseptic

Uses

- to decrease bacteria on the skin that could cause disease
- recommended for repeated use

Warnings

For external use only: hands

Flammable, keep away from fire or flame.

When using this product

- keep out of eyes. In case of contact with eyes, flush thoroughly with water.
- avoid contact with broken skin
- do not inhale or ingest

Stop use and ask a doctor if

- irritation and redness develops
- condition persists for more than 72 hours

Keep out of reach of children.

If swallowed, get medical help or contact a Poison Control Center right away.

Directions

- wet hands thoroughly with product and allow to dry without wiping
- for children under 6, use only under adult supervision
- not recommended for infants

Other information

- do not store above 105⁰F
- may discolor some fabrics
- harmful to wood finishes and plastics

Inactive ingredients

water, glyceryl caprylate/caprate, glycerin, isopropyl myristate, tocopheryl acetate, carbomer or acrylates/C10-30 alkyl acrylate crosspolymer, fragrance, benzophenone-4

Claims

*Effective at eliminating more than 99.99% of many common harmful germs and bacteria in as little as 15 seconds.

Adverse reaction

Distributed by: UpLift Brands, LLC

St. Louis, MO 63114

www.germx.com

Pat. 9,161,982

Principal display panel

germ-x®

SINCE 1997

PLANT BASED

ADVANCED HAND SANITIZER

Kills more than 99.99% of Germs*

MADE WITH PLANT BASED ALCOHOL

with vitamin E

8 FL OZ (236 mL)